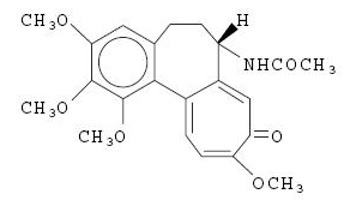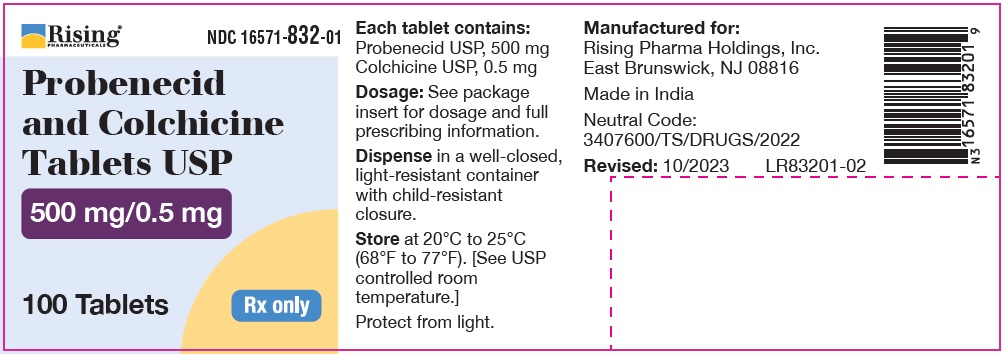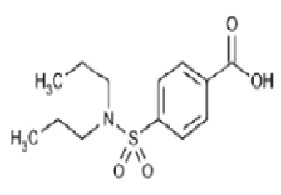 DRUG LABEL: Probenecid and Colchicine
NDC: 16571-832 | Form: TABLET
Manufacturer: Rising Pharma Holdings, Inc.
Category: prescription | Type: Human Prescription Drug Label
Date: 20260127

ACTIVE INGREDIENTS: PROBENECID 500 mg/1 1; COLCHICINE 0.5 mg/1 1
INACTIVE INGREDIENTS: SILICON DIOXIDE; STARCH, CORN; MAGNESIUM STEARATE; MICROCRYSTALLINE CELLULOSE 101; POVIDONE K90; SODIUM LAURYL SULFATE; SODIUM STARCH GLYCOLATE TYPE A POTATO

Probenecid and Colchicine Tablets USP
Rx only

DESCRIPTION

Probenecid and colchicine contains probenecid, which is a uricosuric agent, and colchicine, which has antigout activity, the mechanism of which is unknown. Probenecid is the generic name for p-(Dipropylsulfamoyl)benzoic acid. The structural formula is represented below:

C13H19NO4S M.W.285.36
Probenecid is a white or practically white, fine, crystalline powder. It is soluble in dilute alkali, in alcohol, in chloroform, and in acetone; it is practically insoluble in water and in dilute acids. Colchicine is an alkaloid obtained from various species of Colchicum. The chemical name for Colchicine is (S)-N-(5,6,7,9- tetrahydro-1,2,3,10-tetramethoxy-9-oxobenzo[α]heptalen-7-yl) acetamide. The structural formula is represented below:

C22H25NO6 M.W.399.44
Colchicine consists of yellowish white to pale yellow to pale greenish-yellow powder which darken on exposure to light. Colchicine is freely soluble in chloroform. Each tablet for oral administration contains 500 mg of probenecid and 0.5 mg of colchicine. Each tablet also contains the following inactive ingredients: colloidal silicon dioxide, corn starch, magnesium stearate, microcrystalline cellulose, povidone, sodium lauryl sulfate and sodium starch glycolate.
FDA approved dissolution test specifications differ from the USP.

CLINICAL PHARMACOLOGY

Probenecid is a uricosuric and renal tubular blocking agent. It inhibits the tubular reabsorption of urate, thus increasing the urinary excretion of uric acid and decreasing serum urate levels. Effective uricosuria reduces the miscible urate pool, retards urate deposition, and promotes resorption of urate deposits.

Probenecid inhibits the tubular secretion of penicillin and usually increases penicillin plasma levels by any route the antibiotic is given. A 2-fold to 4-fold elevation has been demonstrated for various penicillins.

Probenecid also has been reported to inhibit the renal transport of many other compounds including amino hippuric acid (PAH), aminosalicylic acid (PAS), indomethacin, sodium iodomethamate and related iodinated organic acids, 17-ketosteroids, pantothenic acid, phenolsulfonphthalein (PSP), sulfonamides, and sulfonylureas. See also Drug Interactions.

Probenecid decreases both hepatic and renal excretion of sulfobromophthalein (BSP). The tubular reabsorption of phosphorus is inhibited in hypoparathyroid but not in euparathyroid individuals.

Probenecid does not influence plasma concentrations of salicylates, nor the excretion of streptomycin, chloramphenicol, chlortetracycline, oxytetracycline, or neomycin.

The mode of action of colchicine in gout is unknown. It is not an analgesic, though it relieves pain in acute attacks of gout. It is not a uricosuric agent and will not prevent progression of gout to chronic gouty arthritis. It does have a prophylactic, suppressive effect that helps to reduce the incidence of acute attacks and to relieve the residual pain and mild discomfort that patients with gout occasionally feel.

In man and certain other animals, colchicine can produce a temporary leukopenia that is followed by leukocytosis.

Colchicine has other pharmacologic actions in animals: It alters neuromuscular function, intensifies gastrointestinal activity by neurogenic stimulation, increases sensitivity to central depressants, heightens response to sympathomimetic compounds, depresses the respiratory center, constricts blood vessels, causes hypertension by central vasomotor stimulation, and lowers body temperature.

INDICATIONS & USAGE

For the treatment of chronic gouty arthritis when complicated by frequent, recurrent acute attacks of gout.

CONTRAINDICATIONS

Hypersensitivity to this product or to probenecid or colchicine.

Probenecid and colchicine tablets are contraindicated in children under 2 years of age.

Not recommended in persons with known blood dyscrasias or uric acid kidney stones.

Therapy with probenecid and colchicine should not be started until an acute gouty attack has subsided.

Pregnancy

Probenecid crosses the placental barrier and appears in cord blood. Colchicine can arrest cell division in animals and plants. In certain species of animals under certain conditions, colchicine has produced teratogenic effects. The possibility of such effects in humans also has been reported. Because of the colchicine component, probenecid and colchicine is contraindicated in pregnant patients. The use of any drug in women of childbearing potential requires that the anticipated benefit be weighed against the possible hazards.

WARNINGS

Exacerbation of gout following therapy with probenecid and colchicine may occur; in such cases additional colchicine or other appropriate therapy is advisable.

Probenecid increases plasma concentrations of methotrexate in both animals and humans. In animal studies, increased methotrexate toxicity has been reported. If probenecid and colchicine is given with methotrexate, the dosage of methotrexate should be reduced and serum levels may need to be monitored.

In patients on probenecid and colchicine the use of salicylates in either small or large doses is contraindicated because it antagonizes the uricosuric action of probenecid. The biphasic action of salicylates in the renal tubules accounts for the so-called “paradoxical effect” of uricosuric agents. In patients on probenecid and colchicine who require a mild analgesic agent the use of acetaminophen rather than small doses of salicylates would be preferred.

Rarely, severe allergic reactions and anaphylaxis have been reported with the use of probenecid and colchicine. Most of these have been reported to occur within several hours after readministration following prior usage of the drug.

The appearance of hypersensitivity reactions requires cessation of therapy with probenecid and colchicine.

Colchicine has been reported to adversely affect spermatogenesis in animals. Reversible azoospermia has been reported in one patient.

PRECAUTIONS

GENERAL PRECAUTIONS

Hematuria, renal colic, costovertebral pain, and formation of uric acid stones associated with the use of probenecid and colchicine in gouty patients may be prevented by alkalization of the urine and a liberal fluid intake (see DOSAGE AND ADMINISTRATION). In these cases when alkali is administered, the acid-base balance of the patient should be watched.

Use with caution in patients with a history of peptic ulcer.

Probenecid and colchicine has been used in patients with some renal impairment but dosage requirements may be increased. Probenecid and colchicine may not be effective in chronic renal insufficiency particularly when the glomerular filtration rate is 30 mL/minute or less.

A reducing substance may appear in the urine of patients receiving probenecid. This disappears with discontinuance of therapy. Suspected glycosuria should be confirmed by using a test specific for glucose.

Adequate animal studies have not been conducted to determine the carcinogenicity potential of probenecid or this drug combination. Since colchicine is an established mutagen, its ability to act as a carcinogen must be suspected and administration of probenecid and colchicine should involve a weighing of the benefit-vs-risk when long-term administration is contemplated.

DRUG INTERACTIONS

When probenecid is used to elevate plasma concentrations of penicillin, or other beta-lactams, or when such drugs are given to patients taking probenecid therapeutically, high plasma concentrations of the other drug may increase the incidence of adverse reactions associated with that drug. In the case of penicillin, or other beta-lactams, psychic disturbances have been reported.

The use of salicylates antagonizes the uricosuric action of probenecid (see WARNINGS). The uricosuric action of probenecid is also antagonized by pyrazinamide.

Probenecid produces an insignificant increase in free sulfonamide plasma concentrations but a significant increase in total sulfonamide plasma levels. Since probenecid decreases the renal excretion of conjugated sulfonamides, plasma concentrations of the latter should be determined from time to time when a sulfonamide and probenecid and colchicine are coadministered for prolonged periods. Probenecid may prolong or enhance the action of oral sulfonylureas and thereby increase the risk of hypoglycemia.

It has been reported that patients receiving probenecid require significantly less thiopental for induction of anesthesia. In addition, ketamine and thiopental anesthesia were significantly prolonged in rats receiving probenecid.

The concomitant administration of probenecid increases the mean plasma elimination half-life of a number of drugs which can lead to increased plasma concentrations. These include agents such as indomethacin, acetaminophen, naproxen, ketoprofen, meclofenamate, lorazepam, and rifampin. Although the clinical significance of this observation has not been established, a lower dosage of the drug may be required to produce a therapeutic effect, and increases in dosage of the drug in question should be made cautiously and in small increments when probenecid is being co-administrated. Although specific instances of toxicity due to this potential interaction have not been observed to date, physicians should be alert to this possibility.

Probenecid given concomitantly with sulindac had only a slight effect on plasma sulfide levels, while plasma levels of sulindac and sulfone were increased. Sulindac was shown to produce a modest reduction in the uricosuric action of probenecid, which probably is not significant under most circumstances.

In animals and in humans, probenecid has been reported to increase plasma concentrations of methotrexate (see WARNINGS).

Falsely high readings for theophylline have been reported in an in vitro study, using the Schack and Waxler technique, when therapeutic concentrations of theophylline and probenecid were added to human plasma.

ADVERSE REACTIONS

The following adverse reactions have been observed and within each category are listed in order of decreasing severity.

Probenecid
Central Nervous System: headache, dizziness.
Metabolic: precipitation of acute gouty arthritis.
Gastrointestinal: hepatic necrosis, vomiting, nausea, anorexia, sore gums.
Genitourinary: nephrotic syndrome, uric acid stones with or without hematuria, renal colic, costovertebral pain, urinary frequency.
Hypersensitivity: anaphylaxis, fever, urticaria, pruritus.
Hematologic: aplastic anemia, leukopenia, hemolytic anemia which in some patients could be related to genetic deficiency of glucose-6-phosphate dehydrogenase in red blood cells, anemia.
Integumentary: dermatitis, alopecia, flushing.

Colchicine
Side effects due to colchicine appear to be a function of dosage. The possibility of increased colchicine toxicity in the presence of hepatic dysfunction should be considered. The appearance of any of the following symptoms may require reduction of dosage or discontinuance of the drug.
Central Nervous System: peripheral neuritis.
Musculoskeletal: muscular weakness.
Gastrointestinal: nausea, vomiting, abdominal pain, or diarrhea may be particularly troublesome in the presence of peptic ulcer or spastic colon.
Hypersensitivity: urticaria.
Hematologic: aplastic anemia, agranulocytosis.
Integumentary: dermatitis, purpura, alopecia.
At toxic doses, colchicine may cause severe diarrhea, generalized vascular damage, and renal damage with hematuria and oliguria.

To report SUSPECTED ADVERSE REACTIONS, contact Rising Pharma Holdings, Inc. at 1-844-874-7464 or FDA at 1-800-FDA-1088 or www.fda.gov/medwatch.

DOSAGE & ADMINISTRATION

Therapy with probenecid and colchicine should not be started until an acute gouty attack has subsided. However, if an acute attack is precipitated during therapy, probenecid and colchicine may be continued without changing the dosage, and additional colchicine or other appropriate therapy should be given to control the acute attack.

The recommended adult dosage is 1 tablet of probenecid and colchicine daily for one week, followed by 1 tablet twice a day thereafter.

Some degree of renal impairment may be present in patients with gout. A daily dosage of 2 tablets may be adequate. However, if necessary, the daily dosage may be increased by 1 tablet every four weeks within tolerance (and usually not above 4 tablets per day) if symptoms of gouty arthritis are not controlled or the 24 hour uric acid excretion is not above 700 mg. As noted, probenecid may not be effective in chronic renal insufficiency particularly when the glomerular filtration rate is 30 mL/minute or less.

Gastric intolerance may be indicative of overdosage, and may be corrected by decreasing the dosage.

As uric acid tends to crystallize out of an acid urine, a liberal fluid intake is recommended, as well as sufficient sodium bicarbonate (3 to 7.5 g daily) or potassium citrate (7.5 g daily) to maintain an alkaline urine (see PRECAUTIONS).

Alkalization of the urine is recommended until the serum urate level returns to normal limits and tophaceous deposits disappear, i.e., during the period when urinary excretion of uric acid is at a high level. Thereafter, alkalization of the urine and the usual restriction of purine-producing foods may be somewhat relaxed.

Probenecid and colchicine (or probenecid) should be continued at the dosage that will maintain normal serum urate levels. When acute attacks have been absent for six months or more and serum urate levels remain within normal limits, the daily dosage of probenecid and colchicine may be decreased by 1 tablet every six months. The maintenance dosage should not be reduced to the point where serum urate levels tend to rise.

HOW SUPPLIED

Probenecid and Colchicine Tablets, USP 500 mg/0.5 mg are bisected, white to off-white capsule shaped, tablets debossed with “C81” on one side and break line on another side.

They are supplied in bottles of 100 count: NDC 16571-832-01

Dispense in a well closed, light-resistant container with child-resistant closure.

Store at 20º to 25ºC (68º to 77ºF); excursions permitted to 15° to 30°C (59° to 86°F) [See USP Controlled Room Temperature].

Protect from light.

Manufactured for:
Rising Pharma Holdings, Inc.
East Brunswick, NJ 08816

Made in India.
Neutral Code: 4323066/TS/DRUGS/2025

Revised: 01/2026

PIR83201-05

PACKAGE LABEL.PRINCIPAL DISPLAY PANEL

NDC 16571-832-01
Probenecid and Colchicine Tablets USP
500 mg/0.5 mg
100 Tablets
Rising Pharma Holdings, Inc.
Rx only